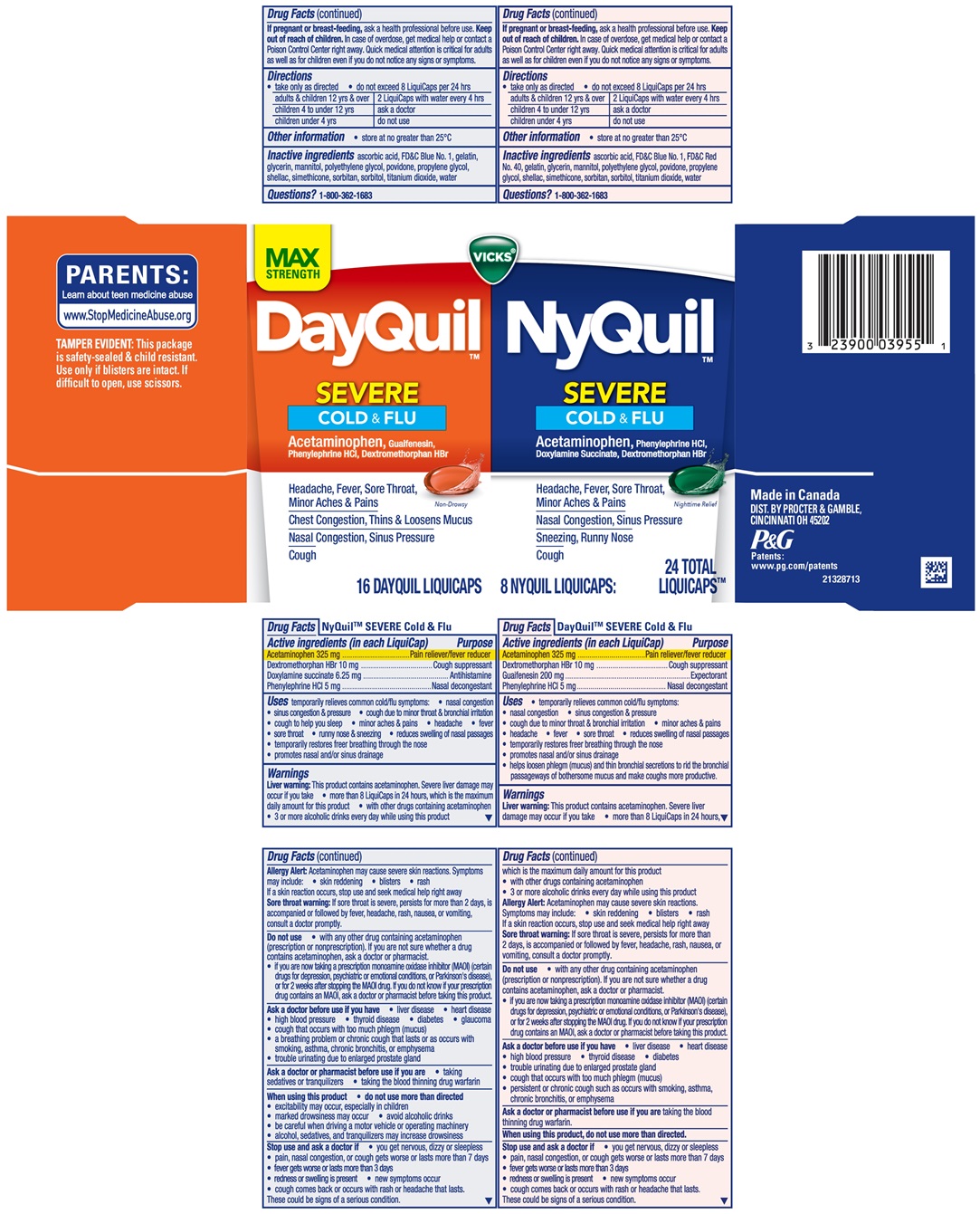 DRUG LABEL: Vicks DayQuil Severe and Vicks NyQuil Severe
NDC: 37000-934 | Form: KIT | Route: ORAL
Manufacturer: The Procter & Gamble Manufacturing Company
Category: otc | Type: HUMAN OTC DRUG LABEL
Date: 20260205

ACTIVE INGREDIENTS: GUAIFENESIN 200 mg/1 1; ACETAMINOPHEN 325 mg/1 1; DEXTROMETHORPHAN HYDROBROMIDE 10 mg/1 1; PHENYLEPHRINE HYDROCHLORIDE 5 mg/1 1; PHENYLEPHRINE HYDROCHLORIDE 5 mg/1 1; ACETAMINOPHEN 325 mg/1 1; DEXTROMETHORPHAN HYDROBROMIDE 10 mg/1 1; DOXYLAMINE SUCCINATE 6.25 mg/1 1
INACTIVE INGREDIENTS: SHELLAC; SORBITOL; FD&C RED NO. 40; FD&C BLUE NO. 1; GELATIN; GLYCERIN; POLYETHYLENE GLYCOL, UNSPECIFIED; POVIDONE; PROPYLENE GLYCOL; WATER; TITANIUM DIOXIDE; DIMETHICONE; MANNITOL; ASCORBIC ACID; SORBITAN; FD&C BLUE NO. 1; GELATIN; GLYCERIN; POLYETHYLENE GLYCOL, UNSPECIFIED; POVIDONE; PROPYLENE GLYCOL; WATER; SORBITOL

Vicks®DayQuil™ Severe and Vicks®NyQuil™ Severe Cold & Flu LiquiCaps™ Convenience Pack

DayQuil™ SEVERE Cold & Flu

Drug Facts

Active ingredients (in each LiquiCap)

Acetaminophen 325 mg
Dextromethorphan HBr 10 mg
Guaifenesin 200 mg
Phenylephrine HCl 5 mg

Purpose

Pain reliever/Fever reducer
Cough suppressant
Expectorant
Nasal decongestant

Uses

temporarily relieves common cold/flu symptoms:

- nasal congestion
- sinus congestion & pressure
- cough due to minor throat & bronchial irritation
- minor aches & pains
- headache
- fever
- sore throat
- reduces swelling of nasal passages
- temporarily restores freer breathing through the nose
- promotes nasal and/or sinus drainage
- helps loosen phlegm (mucus) and thin bronchial secretions to rid the bronchial passageways of bothersome mucus and make coughs more productive.

Warnings

Liver warning:

This product contains acetaminophen.

Severe liver damage may occur if you take

- more than 8 LiquiCaps in 24 hrs, which is the maximum daily amount for this product
- with other drugs containing acetaminophen
- 3 or more alcoholic drinks every day while using this product

Allergy Alert:

Acetaminophen may cause severe skin reactions. Symptoms may include:

- Skin reddening
- Blisters
- Rash

If a skin reaction occurs, stop use and seek medical help right away

Sore throat warning:

If sore throat is severe, persists for more than 2 days, is accompanied or followed by fever, headache, rash, nausea, or vomiting, consult a doctor promptly.

Do not use

- with any other drug containing acetaminophen (prescription or nonprescription). If you are not sure whether a drug contains acetaminophen, ask a doctor or pharmacist.
- if you are now taking a prescription monoamine oxidase inhibitor (MAOI) (certain drugs for depression, psychiatric or emotional conditions, or Parkinson's disease), or for 2 weeks after stopping the MAOI drug. If you do not know if your prescription drug contains an MAOI, ask a doctor or pharmacist before taking this product.

Ask a doctor before use if you have

- liver disease
- heart disease
- high blood pressure
- thyroid disease
- diabetes
- trouble urinating due to enlarged prostate gland
- cough that occurs with too much phlegm (mucus)
- persistent or chronic cough such as occurs with smoking, asthma, chronic bronchitis, or emphysema

Ask a doctor or pharmacist before use if you are taking the blood thinning drug warfarin.

When using this product, do not use more than directed.

Stop use and ask a doctor if

- you get nervous, dizzy or sleepless
- pain, nasal congestion or cough get worse or last more than 7 days
- fever gets worse or lasts more than 3 days
- redness or swelling is present
- new symptoms occur
- cough comes back or occurs with rash or headache that lasts.

These could be signs of a serious condition.

PREGNANCY OR BREAST FEEDING

If pregnant or breast-feeding, ask a health professional before use.

Keep out of reach of children.

In case of overdose, get medical help or contact a Poison Control Center right away. Quick medical attention is critical for adults as well as for children even if you do not notice any signs or symptoms.

Directions

- take only as directed
- do not exceed 8 LiquiCaps per 24 hrs

adults & children 12 yrs & over | 2 LiquiCaps with water every 4 hrs
children 4 to under 12 yrs | ask a doctor
children under 4 yrs | do not use

Other information

- do not exceed 25ºC

Inactive ingredients

ascorbic acid, FD&C Blue no. 1, FD&C Red No. 40, gelatin, glycerin, mannitol, polyethylene glycol, povidone, propylene glycol, shellac, simethicone, sorbitan, sorbitol, titanium dioxide, water

Questions?

1-800-362-1683

NyQuil™ SEVERE Cold & Flu

Drug Facts

Active ingredients (in each LiquiCap)

Acetaminophen 325 mg
Dextromethorphan HBr 10 mg
Doxylamine succinate 6.25 mg

Phenylephrine HCl 5 mg

Purpose

Pain reliever/Fever reducer

Cough suppressant

Antihistamine

Nasal decongestant

Uses

temporarily relieves common cold/flu symptoms:

- nasal congestion
- sinus congestion & pressure
- cough due to minor throat & bronchial irritation
- cough to help you sleep
- minor aches & pains
- headache
- fever
- sore throat
- runny nose & sneezing
- reduces swelling of nasal passages
- temporarily restores freer breathing through the nose
- promotes nasal and/or sinus drainage

Warnings

Liver warning:

This product contains acetaminophen. Severe liver damage may occur if you take

- more than 8 LiquiCaps in 24 hrs, which is the maximum daily amount for this product
- with other drugs containing acetaminophen
- 3 or more alcoholic drinks every day while using this product

Allergy Alert:

Acetaminophen may cause severe skin reactions. Symptoms may include:

- Skin reddening
- Blisters
- Rash

If a skin reaction occurs, stop use and seek medical help right away

Sore throat warning:

If sore throat is severe, persists for more than 2 days, is accompanied or followed by fever, headache, rash, nausea, or vomiting, consult a doctor promptly.

Do not use

- with any other drug containing acetaminophen (prescription or nonprescription). If you are not sure whether a drug contains acetaminophen, ask a doctor or pharmacist.
- if you are now taking a prescription monoamine oxidase inhibitor (MAOI) (certain drugs for depression, psychiatric or emotional conditions, or Parkinson's disease), or for 2 weeks after stopping the MAOI drug. If you do not know if your prescription drug contains an MAOI, ask a doctor or pharmacist before taking this product.

Ask a doctor before use if you have

- liver disease
- heart disease
- high blood pressure
- thyroid disease
- diabetes
- glaucoma
- cough that occurs with too much phlegm (mucus)
- a breathing problem or chronic cough that lasts or as occurs with smoking, asthma, chronic bronchitis or emphysema
- trouble urinating due to enlarged prostate gland

Ask a doctor or pharmacist before use if you are

- taking sedatives or tranquilizers
- taking the blood thinning drug warfarin

When using this product

- do not use more than directed
- excitability may occur, especially in children
- marked drowsiness may occur
- avoid alcoholic drinks
- be careful when driving a motor vehicle or operating machinery
- alcohol, sedatives, & tranquilizers may increase drowsiness

Stop use and ask a doctor if

- you get nervous, dizzy or sleepless
- pain, nasal congestion, or cough gets worse or lasts more than 7 days
- fever gets worse or lasts more than 3 days
- redness or swelling is present
- new symptoms occur
- cough comes back or occurs with rash or headache that lasts.

These could be signs of a serious condition.

If pregnant or breast-feeding,

ask a health professional before use.

Keep out of reach of children.

In case of overdose, get medical help or contact a Poison Control Center right away. Quick medical attention is critical for adults as well as for children even if you do not notice any signs or symptoms.

Directions

- take only as directed
- do not exceed 8 LiquiCaps per 24 hours

adults & children 12 yrs & over | 2 LiquiCaps with water every 4 hrs
children 4 to under 12 yrs | ask a doctor
children under 4 yrs | do not use

Other information

- do not exceed 25°C

Inactive ingredients

ascorbic acid, FD&C Blue No. 1, gelatin, glycerin, mannitol, polyethylene glycol, povidone, propylene glycol, shellac, simethicone, sorbitan, sorbitol, titanium dioxide, water

Questions?

1-800-362-1683

TAMPER EVIDENT:This package is safety-sealed & child resistant. Use only if blisters are intact. If difficult to open, use scissors.

Made in Canada
DIST. BY PROCTER & GAMBLE, CINCINNATI OH 45202

PRINCIPAL DISPLAY PANEL - 24 LIQUICAPS Convenience Pack

MAX

STRENGTH

Vicks ®DayQuil™ Severe and Vicks ®NyQuil™ Severe Cold & Flu LiquiCaps™

VICKS®

DayQuil ™

SEVERE

COLD& FLU
Acetaminophen, Guaifenesin, Phenylephrine HCl, Dextromethorphan HBr

Headache, Fever, Sore Throat, Minor Aches & Pains

Chest Congestion, Thins & Loosens Mucus

Nasal Congestion & Sinus Pressure
Cough

Non-Drowsy

8 DayQuil LiquiCaps

NyQuil ™

SEVERE

COLD& FLU

Acetaminophen, PhenylephrineHCl, Doxylamine Succinate, Dextromethorphan HBr

Headache, Fever, Sore Throat, Minor Aches & Pains

Nasal Congestion, Sinus Pressure

Sneezing, Runny Nose

Cough

Nighttime Relief

16 DAYQUIL LIQUICAPS

8 NYQUIL LIQUICAPS

24 TOTAL LIQUICAPS